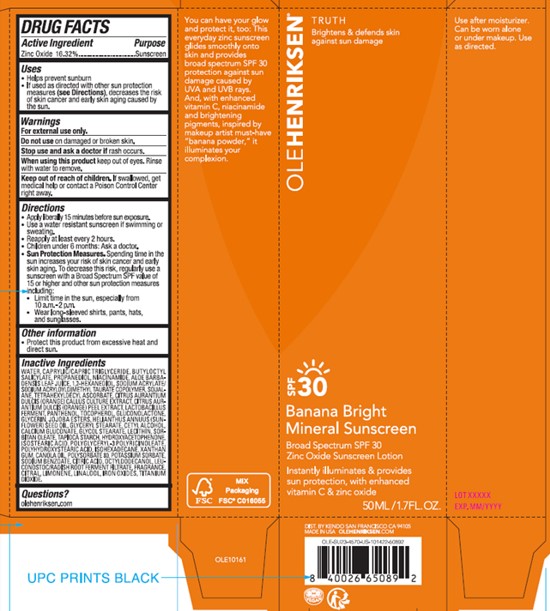 DRUG LABEL: OLE HENRIKSEN BANANA BRIGHT MINERAL SUNSCREEN
NDC: 71499-045 | Form: LOTION
Manufacturer: KENDO HOLDINGS INC
Category: otc | Type: HUMAN OTC DRUG LABEL
Date: 20250930

ACTIVE INGREDIENTS: ZINC OXIDE 16.32 g/100 mL
INACTIVE INGREDIENTS: MEDIUM-CHAIN TRIGLYCERIDES; STARCH, TAPIOCA; OCTYLDODECANOL; POLYGLYCERYL-3 PENTARICINOLEATE; POLYHYDROXYSTEARIC ACID (2300 MW); POLYSORBATE 80; TITANIUM DIOXIDE; BUTYLOCTYL SALICYLATE; PROPANEDIOL; 1,2-HEXANEDIOL; SODIUM ACRYLATE/SODIUM ACRYLOYLDIMETHYLTAURATE COPOLYMER (4000000 MW); TETRAHEXYLDECYL ASCORBATE; SQUALANE; ORANGE; ORANGE PEEL; LIMOSILACTOBACILLUS FERMENTUM; PANTHENOL; GLUCONOLACTONE; ALOE VERA LEAF; GLYCERIN; SORBITAN MONOOLEATE; HYDROGENATED JOJOBA OIL, RANDOMIZED; SUNFLOWER OIL; GLYCERYL MONOSTEARATE; CANOLA OIL; XANTHAN GUM; CITRIC ACID MONOHYDRATE; CETYL ALCOHOL; SODIUM BENZOATE; GLYCOL STEARATE; HYDROXYACETOPHENONE; FERROUS OXIDE; ISOHEXADECANE; LECITHIN, SOYBEAN; LEUCONOSTOC/RADISH ROOT FERMENT FILTRATE; POTASSIUM SORBATE; TOCOPHEROL; BENZYL SALICYLATE; CITRAL; NIACINAMIDE; LIMONENE, (+)-; LINALOOL, (+/-)-; WATER

KENDO (as PLD) - OLE HENRIKSEN BANANA BRIGHT MINERAL SUNSCREEN SPF-30 (71499-045)

ACTIVE INGREDIENTS

ZINC OXIDE 16.32%

PURPOSE

SUNSCREEN

USES

- HELPS PREVENT SUNBURN
- IF USED AS DIRECTED WITH OTHER SUN PROTECTION MEASURES (SEE DIRECTIONS), DECREASES THE RISK OF SKIN CANCER AND EARLY SKIN AGING CAUSED BY THE SUN.

WARNINGS

FOR EXTERNAL USE ONLY.

DO NOT USE ON DAMAGED OR BROKEN SKIN.

STOP USE AND ASK A DOCTOR IF RASH OCCURS.

WHEN USING THIS PRODUCT KEEP OUT OF EYES. RINSE WITH WATER TO REMOVE.

KEEP OUT OF REACH OF CHILDREN. IF SWALLOWED, GET MEDICAL HELP OR CONTACT A POISON CONTROL CENTER RIGHT AWAY.

DIRECTIONS

- APPLY LIBERALLY 15 MINUTES BEFORE SUN EXPOSURE.
- USE A WATER RESISTANT SUNSCREEN IF SWIMMING OR SWEATING.
- REAPPLY AT LEAST EVERY 2 HOURS.
- CHILDREN UNDER 6 MONTHS: ASK A DOCTOR.
- SUN PROTECTION MEASURES. SPENDING TIME IN THE SUN INCREASES YOUR RISK OF SKIN CANCER AND EARLY SKIN AGING. TO DECREASE THIS RISK, REGULARLY USE A SUNCREEN WITH A BROAD SPECTRUM SPF VALUE OF 15 OR HIGHER AND OTHER SUN PROTECTION MEASURES INCLUDING:
- LIMIT TIME IN THE SUN, ESPECIALLY FROM 10 A.M. - 2 P.M.
- WEAR LONG=SLEEVED SHIRTS, PANTS, HATS, AND SUNGLASSES.

OTHER INFORMATION

PROTECT THIS PRODUCT FROM EXCESSIVE HEAT AND DIRECT SUN.

INACTIVE INGREDIENTS

WATER, MEDIUM-CHAIN TRIGLYCERIDES, BUTYLOCTYL SALICYLATE, PROPANEDIOL, NIACINAMIDE, ALOE VERA LEAF, 1,2-HEXANEDIOL, SODIUM ACRYLATE/SODIUM ACRYLOYLDIMETHYLTAURATE COPOLYMER, SQUALANE, TETRAHEXYLDECYL ASCORBATE, ORANGE, ORANGE PEEL, LIMOSILACTOBACILLUS FERMENTUM, PANTHENOL, TOCOPHEROL, GLUCONOLACTONE,

GLYCERIN, JOJOBA ESTERS, SUNFLOWER OIL, GLYCERYL MONOSTEARATE, CETYL ALCOHOL, CALCIUM GLUCONATE, GLYCOL STEARATE, LECITHIN, SORBITAN MONOOLEATE, STARCH, HYDROXYACETOPHENONE, ISOSTEARIC ACID, POLYGLYCERYL-3 POLYRICINOLEATE, POLYHYDROXYSTEARIC ACID, ISOHEXADECANE, XANTHAN GUM, CANOLA OIL, POLYSORBATE 80, POTASSIUM SORBATE, SODIUM BENZOATE, CITRIC ACID, OCTYLDODECANOL, LEUCONOSTOC/RADISH ROOT FERMENT FILTRATE, CITRAL, LIMONENE, LINALOOL, TITANIUM DIOXIDE, IRON OXIDES

QUESTIONS?

OLEHENRIKSEN.COM